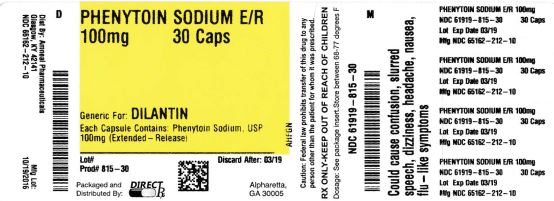 DRUG LABEL: PHENYTOIN SODIUM
NDC: 61919-815 | Form: CAPSULE
Manufacturer: DIRECT RX
Category: prescription | Type: HUMAN PRESCRIPTION DRUG LABEL
Date: 20260227

ACTIVE INGREDIENTS: PHENYTOIN SODIUM 100 mg/1 1

PHENYTOIN SODIUM

DESCRIPTION SECTION

Phenytoin sodium, USP is related to the barbiturates in chemical structure, but has a five-membered ring. The chemical name is sodium 5,5-diphenyl-2,4-imidazolidinedione, having the following structural formula:

[6184a1b4-figure-01]

Each extended phenytoin sodium capsule, USP contains 100 mg phenytoin sodium, USP. Each capsule also contains the following inactive ingredients: D&C Red #28, D&C Red #33, FD&C Blue #1, gelatin, hydroxypropyl cellulose, mannitol, magnesium stearate, talc and titanium dioxide. Product in vivo performance is characterized by a slow and extended rate of absorption with peak blood concentrations expected in 4 to 12 hours as contrasted to Prompt Phenytoin Sodium Capsules, USP with a rapid rate of absorption with peak blood concentration expected in 1½ to 3 hours.

CLINICAL PHARMACOLOGY SECTION

Mechanism of Action

Phenytoin is an antiepileptic drug which can be useful in the treatment of epilepsy. The primary site of action appears to be the motor cortex where spread of seizure activity is inhibited. Possibly by promoting sodium efflux from neurons, phenytoin tends to stabilize the threshold against hyperexcitability caused by excessive stimulation or environmental changes capable of reducing membrane sodium gradient. This includes the reduction of post tetanic potentiation at synapses. Loss of post tetanic potentiation prevents cortical seizure foci from detonating adjacent cortical areas. Phenytoin reduces the maximal activity of brain stem centers responsible for the tonic phase of tonic-clonic (grand mal) seizures.

Pharmacokinetics and Drug Metabolism

The plasma half-life in man after oral administration of phenytoin averages 22 hours, with a range of 7 to 42 hours. Steady-state therapeutic levels are achieved at least 7 to 10 days (5 to 7 half-lives) after initiation of therapy with recommended doses of 300 mg/day.

When serum level determinations are necessary, they should be obtained at least 5 to 7 half-lives after treatment initiation, dosage change, or addition or subtraction of another drug to the regimen so that equilibrium or steady-state will have been achieved. Trough levels provide information about clinically effective serum level range and confirm patient compliance and are obtained just prior to the patient’s next scheduled dose. Peak levels indicate an individual’s threshold for emergence of dose-related side effects and are obtained at the time of expected peak concentration. For extended phenytoin sodium capsules, peak serum levels occur 4 to 12 hours after administration.

Optimum control without clinical signs of toxicity occurs more often with serum levels between 10 and 20 mcg/mL, although some mild cases of tonic-clonic (grand mal) epilepsy may be controlled with lower serum levels of phenytoin.

In most patients maintained at a steady dosage, stable phenytoin serum levels are achieved. There may be wide interpatient variability in phenytoin serum levels with equivalent dosages. Patients with unusually low levels may be noncompliant or hypermetabolizers of phenytoin. Unusually high levels result from liver disease, variant CYP2C9 and CYP2C19 alleles, or drug interactions which result in metabolic interference. The patient with large variations in phenytoin plasma levels, despite standard doses, presents a difficult clinical problem. Serum level determinations in such patients may be particularly helpful. As phenytoin is highly protein bound, free phenytoin levels may be altered in patients whose protein binding characteristics differ from normal.

Most of the drug is excreted in the bile as inactive metabolites which are then reabsorbed from the intestinal tract and excreted in the urine. Urinary excretion of phenytoin and its metabolites occurs partly with glomerular filtration but more importantly by tubular secretion. Because phenytoin is hydroxylated in the liver by an enzyme system which is saturable at high plasma levels, small incremental doses may increase the half-life and produce very substantial increases in serum levels, when these are in the upper range. The steady-state level may be disproportionately increased, with resultant intoxication, from an increase in dosage of 10% or more.

Special Populations

Patients with Renal or Hepatic Disease: Due to an increased fraction of unbound phenytoin in patients with renal or hepatic disease, or in those with hypoalbuminemia, the interpretation of total phenytoin plasma concentrations should be made with caution (see DOSAGE AND ADMINISTRATION). Unbound phenytoin concentrations may be more useful in these patient populations.

Age: Phenytoin clearance tends to decrease with increasing age (20% less in patients over 70 years of age relative to that in patients 20 to 30 years of age). Phenytoin dosing requirements are highly variable and must be individualized (see DOSAGE AND ADMINISTRATION).

Gender and Race: Gender and race have no significant impact on phenytoin pharmacokinetics.

Pediatrics: Initially, 5 mg/kg/day in two or three equally divided doses, with subsequent dosage individualized to a maximum of 300 mg daily. A recommended daily maintenance dosage is usually 4 to 8 mg/kg. Children over 6 years and adolescents may require the minimum adult dose (300 mg/day).

INDICATIONS & USAGE SECTION

Extended phenytoin sodium capsules, USP are indicated for the control of generalized tonic-clonic (grand mal) and complex partial (psychomotor, temporal lobe) seizures and prevention and treatment of seizures occurring during or following neurosurgery.

Phenytoin serum level determinations may be necessary for optimal dosage adjustments (see DOSAGE AND ADMINISTRATION and CLINICAL PHARMACOLOGY sections).

CONTRAINDICATIONS SECTION

Phenytoin, USP is contraindicated in those patients with a history of hypersensitivity to phenytoin, USP, its inactive ingredients, or other hydantoins.

Coadministration of extended phenytoin sodium is contraindicated with delavirdine due to potential for loss of virologic response and possible resistance to delavirdine or to the class of non-nucleoside reverse transcriptase inhibitors.

WARNINGS SECTION

Effects of Abrupt Withdrawal

Abrupt withdrawal of phenytoin in epileptic patients may precipitate status epilepticus. When, in the judgment of the clinician, the need for dosage reduction, discontinuation, or substitution of alternative antiepileptic medication arises, this should be done gradually. In the event of an allergic or hypersensitivity reaction, more rapid substitution of alternative therapy may be necessary. In this case, alternative therapy should be an antiepileptic drug not belonging to the hydantoin chemical class.

Suicidal Behavior and Ideation

Antiepileptic drugs (AEDs), including extended phenytoin sodium, increase the risk of suicidal thoughts or behavior in patients taking these drugs for any indication. Patients treated with any AED for any indication should be monitored for the emergence or worsening of depression, suicidal thoughts or behavior and/or any unusual changes in mood or behavior.

Pooled analyses of 199 placebo-controlled clinical trials (mono- and adjunctive therapy) of 11 different AEDs showed that patients randomized to one of the AEDs had approximately twice the risk (adjusted Relative Risk 1.8, 95% CI:1.2, 2.7) of suicidal thinking or behavior compared to patients randomized to placebo. In these trials, which had a median treatment duration of 12 weeks, the estimated incidence rate of suicidal behavior or ideation among 27,863 AED-treated patients was 0.43%, compared to 0.24% among 16,029 placebo-treated patients, representing an increase of approximately one case of suicidal thinking or behavior for every 530 patients treated. There were four suicides in drug-treated patients in the trials and none in placebo-treated patients, but the number is too small to allow any conclusion about drug effect on suicide.

The increased risk of suicidal thoughts or behavior with AEDs was observed as early as one week after starting drug treatment with AEDs and persisted for the duration of treatment assessed. Because most trials included in the analysis did not extend beyond 24 weeks, the risk of suicidal thoughts or behavior beyond 24 weeks could not be assessed.

The risk of suicidal thoughts or behavior was generally consistent among drugs in the data analyzed. The finding of increased risk with AEDs of varying mechanisms of action and across a range of indications suggests that the risk applies to all AEDs used for any indication. The risk did not vary substantially by age (5 to 100 years) in the clinical trials analyzed.

Table 1 shows absolute and relative risk by indication for all evaluated AEDs.

Table 1 Risk by Indication for Antiepileptic Drugs in the Pooled Analysis
Indication | Placebo Patients with Events Per 1000 Patients | Drug Patients with Events Per 1000 Patients | RelativeRisk: Incidence of Events inDrug Patients/Incidence in Placebo Patients | Risk Difference:Additional DrugPatients with Events Per1000 Patients
Epilepsy | 1 | 3.4 | 3.5 | 2.4
Psychiatric | 5.7 | 8.5 | 1.5 | 2.9
Other | 1 | 1.8 | 1.9 | 0.9
Total | 2.4 | 4.3 | 1.8 | 1.9

The relative risk for suicidal thoughts or behavior was higher in clinical trials for epilepsy than in clinical trials for psychiatric or other conditions, but the absolute risk differences were similar for the epilepsy and psychiatric indications.

Anyone considering prescribing extended phenytoin sodium or any other AED must balance the risk of suicidal thoughts or behavior with the risk of untreated illness. Epilepsy and many other illnesses for which AEDs are prescribed are themselves associated with morbidity and mortality and an increased risk of suicidal thoughts and behavior. Should suicidal thoughts and behavior emerge during treatment, the prescriber needs to consider whether the emergence of these symptoms in any given patient may be related to the illness being treated.

Patients, their caregivers, and families should be informed that AEDs increase the risk of suicidal thoughts and behavior and should be advised of the need to be alert for the emergence or worsening of the signs and symptoms of depression, any unusual changes in mood or behavior, or the emergence of suicidal thoughts, behavior, or thoughts about self-harm. Behaviors of concern should be reported immediately to healthcare providers.

Serious Dermatologic Reactions

Serious and sometimes fatal dermatologic reactions, including toxic epidermal necrolysis (TEN) and Stevens-Johnson syndrome (SJS), have been reported with phenytoin treatment. The onset of symptoms is usually within 28 days, but can occur later. Extended phenytoin sodium should be discontinued at the first sign of a rash, unless the rash is clearly not drug-related. If signs or symptoms suggest SJS/TEN, use of this drug should not be resumed and alternative therapy should be considered. If a rash occurs, the patient should be evaluated for signs and symptoms of Drug Reaction with Eosinophilia and Systemic Symptoms (see DRESS/Multiorgan hypersensitivity below).

Studies in patients of Chinese ancestry have found a strong association between the risk of developing SJS/TEN and the presence of HLA-B*1502, an inherited allelic variant of the HLA B gene, in patients using carbamazepine. Limited evidence suggests that HLA-B*1502 may be a risk factor for the development of SJS/TEN in patients of Asian ancestry taking other antiepileptic drugs associated with SJS/TEN, including phenytoin. Consideration should be given to avoiding phenytoin as an alternative for carbamazepine in patients positive for HLA-B*1502.

The use of HLA-B*1502 genotyping has important limitations and must never substitute for appropriate clinical vigilance and patient management. The role of other possible factors in the development of, and morbidity from, SJS/TEN, such as antiepileptic drug (AED) dose, compliance, concomitant medications, comorbidities and the level of dermatologic monitoring have not been studied.

Drug Reaction with Eosinophilia and Systemic Symptoms (DRESS)/Multiorgan hypersensitivity

Drug Reaction with Eosinophilia and Systemic Symptoms (DRESS), also known as Multiorgan hypersensitivity, has been reported in patients taking antiepileptic drugs, including extended phenytoin sodium. Some of these events have been fatal or life-threatening. DRESS typically, although not exclusively, presents with fever, rash and/or lymphadenopathy, in association with other organ system involvement, such as hepatitis, nephritis, hematological abnormalities, myocarditis, or myositis sometimes resembling an acute viral infection. Eosinophilia is often present. Because this disorder is variable in its expression, other organ systems not noted here may be involved. It is important to note that early manifestations of hypersensitivity, such as fever or lymphadenopathy, may be present even though rash is not evident. If such signs or symptoms are present, the patient should be evaluated immediately. Extended phenytoin sodium should be discontinued if an alternative etiology for the signs or symptoms cannot be established.

Hypersensitivity

Extended phenytoin sodium and other hydantoins are contraindicated in patients who have experienced phenytoin hypersensitivity (see CONTRAINDICATIONS). Additionally, consider alternatives to structurally similar drugs such as carboxamides (e.g., carbamazepine), barbiturates, succinimides and oxazolidinediones (e.g., trimethadione) in these same patients. Similarly, if there is a history of hypersensitivity reactions to these structurally similar drugs in the patient or immediate family members, consider alternatives to extended phenytoin sodium.

Hepatic Injury

Cases of acute hepatotoxicity, including infrequent cases of acute hepatic failure, have been reported with extended phenytoin sodium. These events may be part of the spectrum of DRESS or may occur in isolation. Other common manifestations include jaundice, hepatomegaly, elevated serum transaminase levels, leukocytosis and eosinophilia. The clinical course of acute phenytoin hepatotoxicity ranges from prompt recovery to fatal outcomes. In these patients with acute hepatotoxicity, extended phenytoin sodium should be immediately discontinued and not readministered.

Hematopoietic System

Hematopoietic complications, some fatal, have occasionally been reported in association with administration of extended phenytoin sodium. These have included thrombocytopenia, leukopenia, granulocytopenia, agranulocytosis and pancytopenia with or without bone marrow suppression.

There have been a number of reports suggesting a relationship between phenytoin and the development of lymphadenopathy (local or generalized) including benign lymph node hyperplasia, pseudolymphoma, lymphoma and Hodgkin’s disease. Although a cause and effect relationship has not been established, the occurrence of lymphadenopathy indicates the need to differentiate such a condition from other types of lymph node pathology. Lymph node involvement may occur with or without symptoms and signs of DRESS.

In all cases of lymphadenopathy, follow-up observation for an extended period is indicated and every effort should be made to achieve seizure control using alternative antiepileptic drugs.

Effects on Vitamin D and Bone

The chronic use of phenytoin in patients with epilepsy has been associated with decreased bone mineral density (osteopenia, osteoporosis and osteomalacia) and bone fractures. Phenytoin induces hepatic metabolizing enzymes. This may enhance the metabolism of vitamin D and decrease vitamin D levels, which may lead to vitamin D deficiency, hypocalcemia and hypophosphatemia. Consideration should be given to screening with bone-related laboratory and radiological tests as appropriate and initiating treatment plans according to established guidelines.

Effects of Alcohol Use on Phenytoin Serum Levels

Acute alcoholic intake may increase phenytoin serum levels, while chronic alcohol use may decrease serum levels.

Exacerbation of Porphyria

In view of isolated reports associating phenytoin with exacerbation of porphyria, caution should be exercised in using this medication in patients suffering from this disease.

Usage In Pregnancy:

Clinical:

- Risks to Mother. An increase in seizure frequency may occur during pregnancy because of altered phenytoin pharmacokinetics. Periodic measurement of plasma phenytoin concentrations may be valuable in the management of pregnant women as a guide to appropriate adjustment of dosage (see PRECAUTIONS, Laboratory Tests). However, postpartum restoration of the original dosage will probably be indicated.

- Risks to the Fetus. If this drug is used during pregnancy, or if the patient becomes pregnant while taking the drug, the patient should be apprised of the potential harm to the fetus.

Prenatal exposure to phenytoin may increase the risks for congenital malformations and other adverse developmental outcomes. Increased frequencies of major malformations (such as orofacial clefts and cardiac defects), minor anomalies (dysmorphic facial features, nail and digit hypoplasia), growth abnormalities (including microcephaly) and mental deficiency have been reported among children born to epileptic women who took phenytoin alone or in combination with other antiepileptic drugs during pregnancy. There have also been several reported cases of malignancies, including neuroblastoma, in children whose mothers received phenytoin during pregnancy. The overall incidence of malformations for children of epileptic women treated with antiepileptic drugs (phenytoin and/or others) during pregnancy is about 10%, or two- to three-fold that in the general population. However, the relative contributions of antiepileptic drugs and other factors associated with epilepsy to this increased risk are uncertain and in most cases it has not been possible to attribute specific developmental abnormalities to particular antiepileptic drugs.

Patients should consult with their physicians to weigh the risks and benefits of phenytoin during pregnancy.

Postpartum Period. A potentially life-threatening bleeding disorder related to decreased levels of vitamin K dependent clotting factors may occur in newborns exposed to phenytoin in utero. This drug-induced condition can be prevented with vitamin K administration to the mother before delivery and to the neonate after birth.

Preclinical:

Increased resorption and malformation rates have been reported following administration of phenytoin doses of 75 mg/kg or higher (approximately 120% of the maximum human loading dose or higher on a mg/m2 basis) to pregnant rabbits.

PRECAUTIONS SECTION

General:

The liver is the chief site of biotransformation of phenytoin; patients with impaired liver function, elderly patients, or those who are gravely ill may show early signs of toxicity.

A small percentage of individuals who have been treated with phenytoin have been shown to metabolize the drug slowly. Slow metabolism may be due to limited enzyme availability and lack of induction; it appears to be genetically determined. If early signs of dose-related CNS toxicity develop, plasma levels should be checked immediately.

Hyperglycemia, resulting from the drug’s inhibitory effects on insulin release, has been reported. Phenytoin may also raise the serum glucose level in diabetic patients.

Phenytoin is not indicated for seizures due to hypoglycemic or other metabolic causes. Appropriate diagnostic procedures should be performed as indicated.

Phenytoin is not effective for absence (petit mal) seizures. If tonic-clonic (grand mal) and absence (petit mal) seizures are present, combined drug therapy is needed.

Serum levels of phenytoin sustained above the optimal range may produce confusional states referred to as “delirium,” “psychosis,” or “encephalopathy,” or rarely irreversible cerebellar dysfunction. Accordingly, at the first sign of acute toxicity, plasma levels are recommended. Dose reduction of phenytoin therapy is indicated if plasma levels are excessive; if symptoms persist, termination is recommended. (See WARNINGS section.)

Information for Patients

Inform patients of the availability of a Medication Guide, and instruct them to read the Medication Guide prior to taking extended phenytoin sodium. Instruct patients to take extended phenytoin sodium only as prescribed.

Patients taking phenytoin should be advised of the importance of adhering strictly to the prescribed dosage regimen, and of informing the physician of any clinical condition in which it is not possible to take the drug orally as prescribed, e.g., surgery, etc.

Patients should be made aware of the early toxic signs and symptoms of potential hematologic, dermatologic, hypersensitivity, or hepatic reactions. These symptoms may include, but are not limited to, fever, sore throat, rash, ulcers in the mouth, easy bruising, lymphadenopathy and petechial or purpuric hemorrhage, and in the case of liver reactions, anorexia, nausea/vomiting, or jaundice. The patient should be advised that, because these signs and symptoms may signal a serious reaction, that they must report any occurrence immediately to a physician. In addition, the patient should be advised that these signs and symptoms should be reported even if mild or when occurring after extended use.

Patients should also be cautioned on the use of other drugs or alcoholic beverages without first seeking the physician’s advice.

The importance of good dental hygiene should be stressed in order to minimize the development of gingival hyperplasia and its complications.

Patients, their caregivers, and families should be counseled that AEDs, including extended phenytoin sodium, may increase the risk of suicidal thoughts and behavior and should be advised of the need to be alert for the emergence or worsening of symptoms of depression, any unusual changes in mood or behavior, or the emergence of suicidal thoughts, behavior, or thoughts about self-harm. Behaviors of concern should be reported immediately to healthcare providers.

Patients should be encouraged to enroll in the North American Antiepileptic Drug (NAAED) Pregnancy Registry if they become pregnant. This registry is collecting information about the safety of antiepileptic drugs during pregnancy. To enroll, patients can call the toll free number 1-888-233-2334 (see PRECAUTIONS: Pregnancy section).

Do not use capsules which are discolored.

Laboratory Tests:

Phenytoin serum level determinations may be necessary to achieve optimal dosage adjustments. Phenytoin doses are usually selected to attain therapeutic plasma total phenytoin concentrations of 10 to 20 mcg/mL (unbound phenytoin concentrations of 1 to 2 mcg/mL).

Drug Interactions:

Phenytoin is extensively bound to serum plasma proteins and is prone to competitive displacement. Phenytoin is metabolized by hepatic cytochrome P450 enzymes CYP2C9 and CYP2C19, and is particularly susceptible to inhibitory drug interactions because it is subject to saturable metabolism. Inhibition of metabolism may produce significant increases in circulating phenytoin concentrations and enhance the risk of drug toxicity. Phenytoin is a potent inducer of hepatic drug-metabolizing enzymes. Serum level determinations for phenytoin are especially helpful when possible drug interactions are suspected.

The most commonly occurring drug interactions are listed below:

Note: The list is not intended to be inclusive or comprehensive. Individual drug package inserts should be consulted.

Drugs that affect phenytoin concentrations:

- Drugs that may increase phenytoin serum levels include: acute alcohol intake, amiodarone, anti-epileptic agents (ethosuximide, felbamate, oxcarbazepine, methsuximide, topiramate), azoles (fluconazole, ketoconazole, itraconazole, voriconazole), capecitabine, chloramphenicol, chlordiazepoxide, diazepam, disulfiram, estrogens, fluorouracil, fluoxetine, fluvastatin, fluvoxamine, H2-antagonists (e.g. cimetidine), halothane, isoniazid, methylphenidate, omeprazole, phenothiazines, salicylates, sertraline, succinimides, sulfonamides (e.g., sulfamethizole, sulfaphenazole, sulfadiazine, sulfamethoxazole-trimethoprim), ticlopidine, tolbutamide, trazodone and warfarin.
- Drugs that may decrease phenytoin levels, include: anti-cancer drugs usually in combination (e.g., bleomycin, carboplatin, cisplatin, doxorubicin, methotrexate) carbamazepine, chronic alcohol abuse, folic acid, fosamprenavir, nelfinavir, reserpine, ritonavir, St. John’s Wort, sucralfate and vigabatrin.
- Administration of phenytoin with preparations that increase gastric pH (e.g., supplements or antacids containing calcium carbonate, aluminum hydroxide and magnesium hydroxide) may affect the absorption of phenytoin. In most cases where interactions were seen, the effect is a decrease in phenytoin levels when the drugs are taken at the same time. When possible, phenytoin and these products should not be taken at the same time of day.
- Drugs that may either increase or decrease phenytoin serum levels, include: phenobarbital, sodium valproate and valproic acid. Similarly, the effect of phenytoin on phenobarbital, valproic acid and sodium valproate serum levels is unpredictable.
- The addition or withdrawal of these agents in patients on phenytoin therapy may require an adjustment of the phenytoin dose to achieve optimal clinical outcome.

Drugs affected by phenytoin:

- Drugs that should not be coadministered with phenytoin: Delavirdine (see CONTRAINDICATIONS).
- Drugs whose efficacy is impaired by phenytoin include: azoles (fluconazole, ketoconazole, itraconazole, voriconazole, posaconazole), corticosteroids, doxycycline, estrogens, furosemide, irinotecan, oral contraceptives, paclitaxel, paroxetine, quinidine, rifampin, sertraline, teniposide, theophylline and vitamin D.
- Increased and decreased PT/INR responses have been reported when phenytoin is coadministered with warfarin.
- Phenytoin decreases plasma concentrations of active metabolites of albendazole, certain HIV antivirals (efavirenz, lopinavir/ritonavir, indinavir, nelfinavir, ritonavir, saquinavir), anti-epileptic agents (felbamate, topiramate, oxcarbazepine, quetiapine) atorvastatin, cyclosporine, digoxin, fluvastatin, folic acid, mexiletine, nisoldipine, praziquantel and simvastatin.
- Phenytoin when given with fosamprenavir alone may decrease the concentration of amprenavir, the active metabolite. Phenytoin when given with the combination of fosamprenavir and ritonavir may increase the concentration of amprenavir.
- Resistance to the neuromuscular blocking action of the non-depolarizing neuromuscular blocking agents pancuronium, vecuronium, rocuronium and cisatracurium has occurred in patients chronically administered phenytoin. Whether or not phenytoin has the same effect on other non-depolarizing agents is unknown. Patients should be monitored closely for more rapid recovery from neuromuscular blockade than expected, and infusion rate requirements may be higher.
- The addition or withdrawal of phenytoin during concomitant therapy with these agents may require adjustment of the dose of these agents to achieve optimal clinical outcome.

Drug Enteral Feeding/Nutritional Preparations Interaction:

Literature reports suggest that patients who have received enteral feeding preparations and/or related nutritional supplements have lower than expected phenytoin plasma levels. It is therefore suggested that phenytoin not be administered concomitantly with an enteral feeding preparation. More frequent serum phenytoin level monitoring may be necessary in these patients.

Drug/Laboratory Test Interactions:

Phenytoin may decrease serum concentrations of T4. It may also produce lower than normal values for dexamethasone or metyrapone tests. Phenytoin may cause increased serum levels of glucose, alkaline phosphatase and gamma glutamyl transpeptidase (GGT).

Care should be taken when using immunoanalytical methods to measure plasma phenytoin concentrations.

Carcinogenesis:

See WARNINGS section for information on carcinogenesis.

Pregnancy: Pregnancy Category D; See WARNINGS section.

To provide information regarding the effects of in utero exposure to extended phenytoin sodium, physicians are advised to recommend that pregnant patients taking extended phenytoin sodium enroll in the North American Antiepileptic Drug (NAAED) Pregnancy Registry. This can be done by calling the toll free number 1-888-233-2334, and must be done by patients themselves. Information on the registry can also be found at the website http://www.aedpregnancyregistry.org/.

Nursing Mothers:

Infant breast-feeding is not recommended for women taking this drug because phenytoin appears to be secreted in low concentrations in human milk.

Pediatric Use: See DOSAGE AND ADMINISTRATION section.

Geriatric Use: Phenytoin clearance tends to decrease with increasing age (see CLINICAL PHARMACOLOGY: Special Populations).

ADVERSE REACTIONS SECTION

Body as a Whole: Allergic reactions in the form of rash and rarely more serious forms (see Skin and Appendages paragraph below) and DRESS (see WARNINGS) have been observed. Anaphylaxis has also been reported.

There have also been reports of coarsening of facial features, systemic lupus erythematosus, periarteritis nodosa and immunoglobulin abnormalities.

Nervous System: The most common manifestations adverse reactions encountered with phenytoin therapy are referable to this nervous system reactions and are usually dose-related. These Reactions include nystagmus, ataxia, slurred speech, decreased coordination, somnolence and mental confusion. Dizziness, vertigo, insomnia, transient nervousness, motor twitchings, paresthesias and headaches have also been observed. There have also been rare reports of phenytoin induced dyskinesias, including chorea, dystonia, tremor and asterixis, similar to those induced by phenothiazine and other neuroleptic drugs.

A predominantly sensory peripheral polyneuropathy has been observed in patients receiving long-term phenytoin therapy.

Digestive System: Acute hepatic failure, toxic hepatitis, liver damage, Nnausea, vomiting, constipation, enlargement of the lips,and gingival hyperplasia, toxic hepatitis and liver damage.

Skin and Appendages: Dermatological manifestations sometimes accompanied by fever have included scarlatiniform or morbilliform rashes. A morbilliform rash (measles-like) is the most common; other types of dermatitis are seen more rarely. Other more serious forms which may be fatal have included bullous, exfoliative or purpuric dermatitis, Stevens-Johnson syndrome and toxic epidermal necrolysis (see WARNINGS section). There have also been reports of hypertrichosis.

Hematologic and Lymphatic System: Hematopoietic complications, some fatal, have occasionally been reported in association with administration of phenytoin. These have included thrombocytopenia, leukopenia, granulocytopenia, agranulocytosis and pancytopenia with or without bone marrow suppression. While macrocytosis and megaloblastic anemia have occurred, these conditions usually respond to folic acid therapy. Lymphadenopathy including benign lymph node hyperplasia, pseudolymphoma, lymphoma and Hodgkin’s disease have been reported (see WARNINGS section).

Special Senses: Altered taste sensation including metallic taste.

Urogenital: Peyronie’s disease.

OVERDOSAGE SECTION

The lethal dose in pediatric patients is not known. The lethal dose in adults is estimated to be 2 to 5 grams. The initial symptoms are nystagmus, ataxia and dysarthria. Other signs are tremor, hyperreflexia, lethargy, slurred speech, nausea, vomiting. The patient may become comatose and hypotensive. Death is due to respiratory and circulatory depression.

There are marked variations among individuals with respect to phenytoin plasma levels where toxicity may occur. Nystagmus, on lateral gaze, usually appears at 20 mcg/mL, ataxia at 30 mcg/mL; dysarthria and lethargy appear when the plasma concentration is over 40 mcg/mL, but as high a concentration as 50 mcg/mL has been reported without evidence of toxicity. As much as 25 times the therapeutic dose has been taken to result in a serum concentration over 100 mcg/mL with complete recovery.

Treatment:

Treatment is nonspecific since there is no known antidote.

The adequacy of the respiratory and circulatory systems should be carefully observed and appropriate supportive measures employed. Hemodialysis can be considered since phenytoin is not completely bound to plasma proteins. Total exchange transfusion has been used in the treatment of severe intoxication in pediatric patients.

In acute overdosage, the possibility of other CNS depressants, including alcohol, should be borne in mind.

DOSAGE & ADMINISTRATION SECTION

Serum concentrations should be monitored in changing from extended phenytoin sodium capsules, USP to Prompt Phenytoin Sodium Capsules, USP, and from the sodium salt to the free acid form.

Extended phenytoin sodium capsules, USP are formulated with the sodium salt of phenytoin. Because there is approximately an 8% increase in drug content with the free acid form over that of the sodium salt, dosage adjustments and serum level monitoring may be necessary when switching from a product formulated with the free acid to a product formulated with the sodium salt and vice versa.

General:

Dosage should be individualized to provide maximum benefit. In some cases, serum blood level determinations may be necessary for optimal dosage adjustments—the clinically effective serum level is usually 10 to 20 mcg/mL. With recommended dosage, a period of seven to ten days may be required to achieve steady-state blood levels with phenytoin and changes in dosage (increase or decrease) should not be carried out at intervals shorter than seven to ten days.

Adult Dosage:

Divided daily dosage:

Patients who have received no previous treatment may be started on one 100-mg extended phenytoin sodium capsule, USP three times daily and the dosage then adjusted to suit individual requirements. For most adults, the satisfactory maintenance dosage will be one capsule three to four times a day. An increase up to two capsules three times a day may be made, if necessary.

Once-a-day dosage:

In adults, if seizure control is established with divided doses of three 100-mg extended phenytoin sodium capsules, USP daily, once-a-day dosage with 300 mg of extended phenytoin sodium capsules, USP may be considered. Studies comparing divided doses of 300 mg with a single daily dose of this quantity indicated absorption, peak plasma levels, biologic half-life, difference between peak and minimum values, and urinary recovery were equivalent. Once-a-day dosage offers a convenience to the individual patient or to nursing personnel for institutionalized patients and is intended to be used only for patients requiring this amount of drug daily. A major problem in motivating noncompliant patients may also be lessened when the patient can take this drug once a day. However, patients should be cautioned not to miss a dose, inadvertently.

Only extended phenytoin sodium capsules, USP are recommended for once-a-day dosing. Inherent differences in dissolution characteristics and resultant absorption rates of phenytoin due to different manufacturing procedures and/or dosage forms preclude such recommendation for other phenytoin products. When a change in the dosage form or brand is prescribed, careful monitoring of phenytoin serum levels should be carried out.

Loading dose:

Some authorities have advocated use of an oral loading dose of phenytoin in adults who require rapid steady-state serum levels and where intravenous administration is not desirable. This dosing regimen should be reserved for patients in a clinic or hospital setting where phenytoin serum levels can be closely monitored. Patients with a history of renal or liver disease should not receive the oral loading regimen.

Initially, one gram of extended phenytoin sodium capsules, USP is divided into three doses (400 mg, 300 mg, 300 mg) and administered at two-hour intervals. Normal maintenance dosage is then instituted 24 hours after the loading dose, with frequent serum level determinations.

Dosing in Special Populations

Patients with Renal or Hepatic Disease: Due to an increased fraction of unbound phenytoin in patients with renal or hepatic disease, or in those with hypoalbuminemia, the interpretation of total phenytoin plasma concentrations should be made with caution. Unbound phenytoin concentrations may be more useful in these patient populations.

Elderly Patients: Phenytoin clearance is decreased slightly in elderly patients and lower or less frequent dosing may be required.

Pediatric: Initially, 5 mg/kg/day in two or three equally divided doses, with subsequent dosage individualized to a maximum of 300 mg daily. A recommended daily maintenance dosage is usually 4 to 8 mg/kg. Children over 6 years old and adolescents may require the minimum adult dose (300 mg/day).

HOW SUPPLIED SECTION

Extended Phenytoin Sodium Capsules, USP 100 mg are supplied as white opaque / light lavender opaque, hard gelatin capsules imprinted with "IP 212" on both cap and body.

They are available as follows:

Bottles of 30: NDC 65162-212-03

Bottles of 100: NDC 65162-212-10

Bottles of 500: NDC 65162-212-50

Bottles of 1000: NDC 65162-212-11

Store at 20° to 25°C (68° to 77°F) [See USP Controlled Room Temperature]. Preserve in tight, light-resistant containers. Protect from moisture.

Rx only

SPL MEDGUIDE SECTION

- Extended Phenytoin (FEN-i-toyn) Sodium Capsules
  Read this Medication Guide before you start taking extended phenytoin sodium capsules and each time you get a refill. There may be new information. This information does not take the place of talking to your healthcare provider about your medical condition or treatment. If you have any questions about extended phenytoin sodium capsules, ask your healthcare provider or pharmacist.
  What is the most important information I should know about extendedphenytoin sodium capsules?
  Do not stop taking extended phenytoin sodium capsules without first talking to your healthcare provider. Stopping extended phenytoin sodium capsules suddenly can cause serious problems.
  Extended phenytoin sodium capsules can cause serious side effects including:
  1. Like other antiepileptic drugs, extended phenytoin sodium capsules may cause suicidal thoughts or actions in a very small number of people, about 1 in 500.
  Call a healthcare provider right away if you have any of these symptoms, especially if they are new, worse, or worry you:
  - thoughts about suicide or dying
  - attempts to commit suicide
  - new or worse depression
  - new or worse anxiety
  - feeling agitated or restless
  - panic attacks
  - trouble sleeping (insomnia)
  - new or worse irritability
  - acting aggressive, being angry, or violent
  - acting on dangerous impulses
  - an extreme increase in activity and talking (mania)
  - other unusual changes in behavior or mood
  How can I watch for early symptoms of suicidal thoughts and actions?
  - Pay attention to any changes, especially sudden changes, in mood, behaviors, thoughts, or feelings.
  - Keep all follow-up visits with your healthcare provider as scheduled.
  Call your healthcare provider between visits as needed, especially if you are worried about
  symptoms.
  Do not stop taking extended phenytoin sodium capsules without first talking to a healthcare provider.
  Stopping extended phenytoin sodium capsules suddenly can cause serious problems. Stopping a seizure medicine suddenly in a patient who has epilepsy can cause seizures that will not stop (status epilepticus).
  Suicidal thoughts or actions can be caused by things other than medicines. If you have suicidal
  thoughts or actions, your healthcare provider may check for other causes.
  2. Extended phenytoin sodium capsules may harm your unborn baby.
  - If you take extended phenytoin sodium capsules during pregnancy, your baby is at risk for serious birth defects.
  - Birth defects may occur even in children born to women who are not taking any medicines and do not have other risk factors.
  - If you take extended phenytoin sodium capsules during pregnancy, your baby is also at risk for bleeding problems right after birth. Your healthcare provider may give you and your baby medicine to prevent this.
  - All women of child-bearing age should talk to their healthcare provider about using other possible treatments instead of extended phenytoin sodium capsules. If the decision is made to use extended phenytoin sodium capsules, you should use effective birth control (contraception) unless you are planning to become pregnant.
  - Tell your healthcare provider right away if you become pregnant while taking extended phenytoin sodium capsules. You and your healthcare provider should decide if you will take extended phenytoin sodium capsules while you are pregnant.
  - Pregnancy Registry: If you become pregnant while taking extended phenytoin sodium capsules, talk to your healthcare provider about registering with the North American Antiepileptic Drug Pregnancy Registry. You can enroll in this registry by calling 1-888-233-2334. The purpose of this registry is to collect information about the safety of antiepileptic drugs during pregnancy.
  3. Swollen glands (lymph nodes)
  4. Allergic reactions or serious problems which may affect organs and other parts of your body like the liver or blood cells. You may or may not have a rash with these types of reactions. Symptoms can include any of the following:
  - swelling of your face, eyes, lips, or tongue
  - trouble swallowing or breathing
  - a skin rash
  - hives
  - fever, swollen glands (lymph nodes), or sore throat that do not go away or come and go
  - painful sores in the mouth or around your eyes
  - yellowing of your skin or eyes
  - bruising or bleeding
  - severe fatigue or weakness
  - severe muscle pain
  - frequent infections or an infection that does not go away
  - loss of appetite (anorexia)
  - nausea or vomiting
  Call your healthcare provider right away if you have any of the symptoms listed above.
  What are extended phenytoin sodium capsules?
  Extended phenytoin sodium capsules are a prescription medicine used to treat tonic-clonic (grand mal), complex partial (psychomotor or temporal lobe) seizures, and to prevent and treat seizures that happen during or after brain surgery.
  Who should not take extended phenytoin sodium capsules?
  Do not take extended phenytoin sodium capsules if you:
  - are allergic to phenytoin or any of the ingredients in extended phenytoin sodium capsules. See the end of this leaflet for a complete list of ingredients in extended phenytoin sodium capsules.
  - have had an allergic reaction to CEREBYX (fosphenytoin), PEGANONE (ethotoin), or MESANTOIN (mephenytoin).
  - take delavirdine
  What should I tell my healthcare provider before taking extended phenytoin sodium capsules?
  Before you take extended phenytoin sodium capsules, tell your healthcare provider if you:
  - Have or had liver disease
  - Have or had porphyria
  - Have or had diabetes
  - Have or have had depression, mood problems, or suicidal thoughts or behavior
  - Are pregnant or plan to become pregnant. If you become pregnant while taking extended phenytoin sodium capsules, the level of extended phenytoin sodium in your blood may decrease, causing your seizures to become worse. Your healthcare provider may change your dose of extended phenytoin sodium capsules.
  - Are breast feeding or plan to breastfeed. Extended phenytoin sodium can pass into breast milk. You and your healthcare provider should decide if you will take extended phenytoin sodium capsules or breastfeed. You should not do both.
  Tell your healthcare provider about all the medicines you take, including prescription and
  - non-prescription medicines, vitamins and herbal supplements.
    Taking extended phenytoin sodium capsules with certain other medicines can cause side effects or affect how well they work. Do not start or stop other medicines without talking to your healthcare provider.
    +Know the medicines you take. Keep a list of them and show it to your healthcare provider and pharmacist when you get a new medicine.
    How should I take extended phenytoin sodium capsules?
  - Take extended phenytoin sodium capsules exactly as prescribed. Your healthcare provider will tell you how much extended phenytoin sodium capsules to take.
  - Your healthcare provider may change your dose. Do not change your dose of extended phenytoin sodium capsules without talking to your healthcare provider.
  - Extended phenytoin sodium capsules can cause overgrowth of your gums. Brushing and flossing your teeth and seeing a dentist regularly while taking extended phenytoin sodium capsules can help prevent this.
  - If you take too much extended phenytoin sodium capsules, call your healthcare provider or local Poison Control Center right away.
  - Do not stop taking extended phenytoin sodium capsules without first talking to your healthcare provider. Stopping extended phenytoin sodium capsules suddenly can cause serious problems.
  What should I avoid while taking extended phenytoin sodium capsules?
  - Do not drink alcohol while you take extended phenytoin sodium capsules without first talking to your healthcare provider. Drinking alcohol while taking extended phenytoin sodium capsules may change your blood levels of extended phenytoin sodium capsules which can cause serious problems.
  - Do not drive, operate heavy machinery, or do other dangerous activities until you know how extended phenytoin sodium capsules affect you. Extended phenytoin sodium capsules can slow your thinking and motor skills.
  What are the possible side effects of extended phenytoin sodium capsules?
  See “What is the most important information I should know about extended phenytoin sodium capsules?”
  Extended phenytoin sodium capsules may cause other serious side effects including:
  - Softening of your bones (osteopenia, osteoporosis and osteomalacia). This can cause broken bones.
    Call your healthcare provider right away, if you have any of the symptoms listed above.
    The most common side effects of extended phenytoin sodium capsules include:
  - problems with walking and coordination
  - slurred speech
  - confusion
  - dizziness
  - trouble sleeping
  - nervousness
  - tremor
  - headache
  - nausea
  - vomiting
  - constipation
  - rash
  These are not all the possible side effects of extended phenytoin sodium capsules. For more information, ask your healthcare provider or pharmacist.
  Tell your healthcare provider if you have any side effect that bothers you or that does not go away.
  Call your doctor for medical advice about side effects. You may report side effects to FDA at 1-800-FDA-1088.
  How should I store extended phenytoin sodium capsules?
  - Store extended phenytoin sodium capsules at room temperature between 68°F to 77°F (20°C to 25°C) in tight, light-resistant containers. Protect from moisture.
  Keep extended phenytoin sodiumcapsules and all medicines out of the reach of children.
  General information about extended phenytoin sodium capsules
  Medicines are sometimes prescribed for purposes other than those listed in a Medication Guide. Do not use extended phenytoin sodium capsules for a condition for which it was not prescribed. Do not give extended phenytoin sodium capsules to other people, even if they have the same symptoms that you have. It may harm them.
  This Medication Guide summarizes the most important information about extended phenytoin sodium capsules. If you would like more information, talk with your healthcare provider. You can ask your healthcare provider or pharmacist for information about extended phenytoin sodium capsules that was written for healthcare professionals.
  For more information about extended phenytoin sodium capsules, visit www.amneal.com or call 1-877-835-5472.
  What are the ingredients in extended phenytoin sodium capsules?
  Extended Oral Capsule
  Extended phenytoin sodium capsule 100mg: White opaque/lavender opaque, hard gelatin capsules imprinted “IP 212” on both cap and body.
  Active ingredient: 100 mg phenytoin sodium
  Inactive ingredients: D&C Red #28, D&C Red #33, FD&C Blue #1, gelatin, hydroxypropyl cellulose, mannitol, magnesium stearate, talc and titanium dioxide.
  This Medication Guide has been approved by the U.S. Food and Drug Administration.
  Close